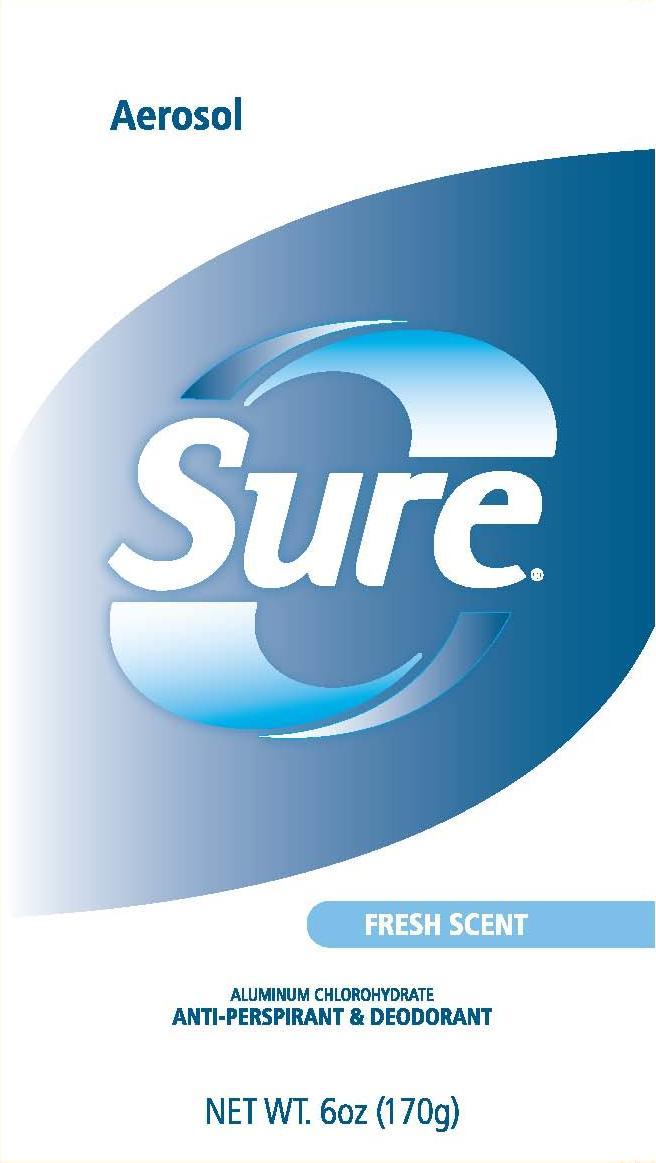 DRUG LABEL: Sure Antiperspirant Deodorant Fresh
NDC: 41595-5519 | Form: AEROSOL
Manufacturer: Idelle Labs, Ltd
Category: otc | Type: HUMAN OTC DRUG LABEL
Date: 20111129

ACTIVE INGREDIENTS: ALUMINUM CHLOROHYDRATE 12 g/100 g
INACTIVE INGREDIENTS: BUTANE; CYCLOMETHICONE 5; ISOPROPYL MYRISTATE; DIMETHICONE; HECTORITE

Sure Aerosol Antiperspirant Deodorant Fresh Scent

Aerosol

Sure Fresh Scent
Aluminum Chlorohydrate
Anti-perspirant & Deodorant

Shake well before use.

Active ingredient

Aluminum Chlorohydrate 10% (anhydrous)

Purpose

Antiperspirant

Use

reduces underarm wetness

Warnings

For external use only.

Flammable

-do not spray ear flame or while smoking-contents under pressure
-do not crush, puncture or incinerate
-do not store at temperature above 120 F

Do not use

on broken skin

Ask a doctor before use if you have

kidney disease

When using this product

-keep away from face and mouth to avoid breathing it.
-avoid spraying in eyes
-use only as directed; intentional misuse by deliberately concentrating and inhaling the contents can be harmful or fatal

Stop use if

rash or irritation occurs

Keep out of reach of children.

If swallowed, get medical help or contact a Poison Control Center right away.

Directions

-apply to underarms only
-shake well before each use-hold can about 6 inches away from underarm and spray.

Inactive ingredients

Butane, Hydrofluorocarbon 152a, Cyclopentasiloxane, Isopropyl Myristate, Dimethicone, Disteardimonium Hectorite, Propylene Carbonate, Fragrance

Questions?

www.sureap.com 1-800-487-7273
©2011 Idelle Labs, Ltd. All rights reserved
Made in the USA and distributed by Idelle Labs, Ltd., El Paso, TX 79912. Sure® is a registered trademark of Helen of Troy Limited

label